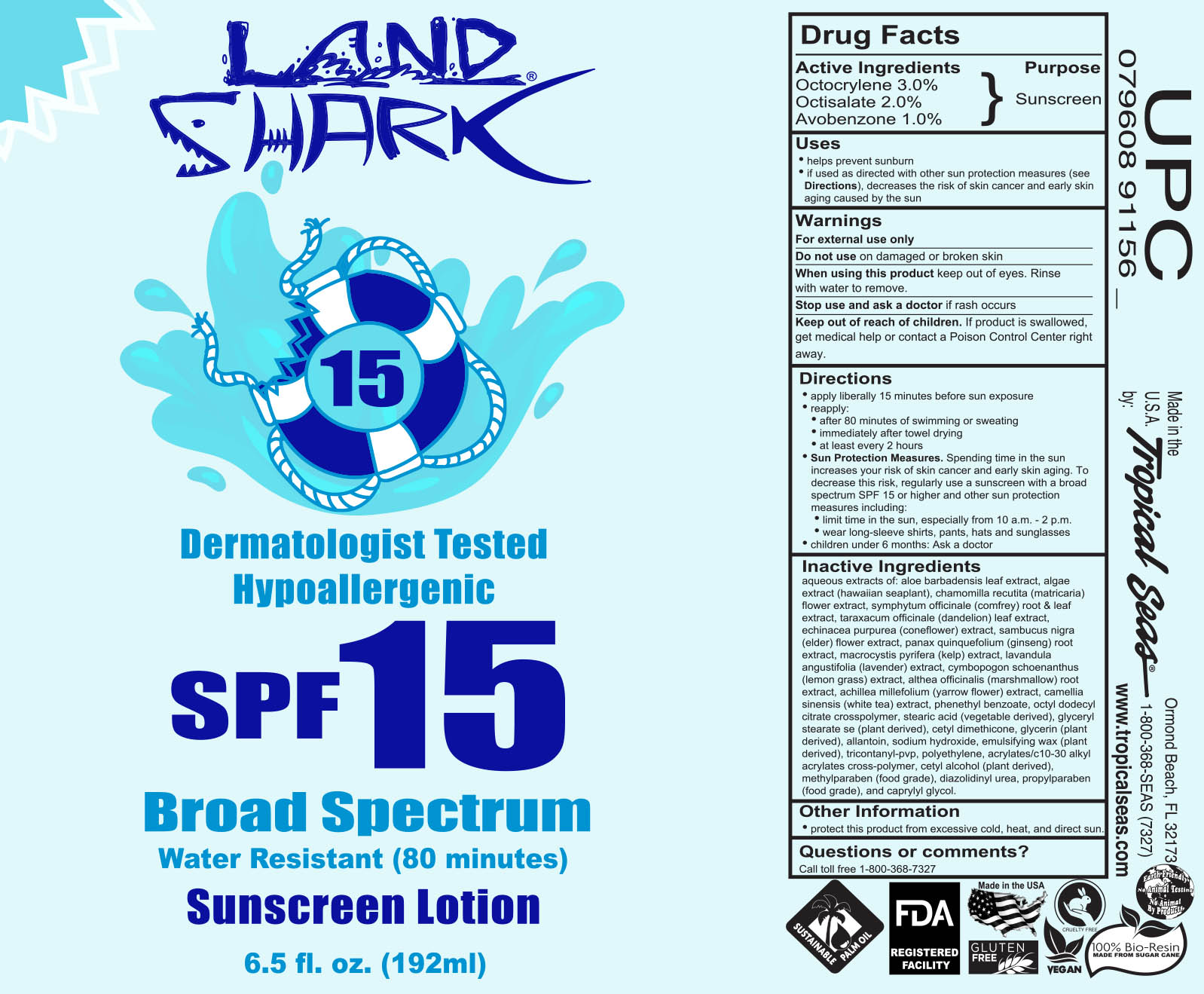 DRUG LABEL: Land Shark SPF 15
NDC: 52854-915 | Form: LOTION
Manufacturer: Tropical Seas, Inc.
Category: otc | Type: HUMAN OTC DRUG LABEL
Date: 20251104

ACTIVE INGREDIENTS: OCTOCRYLENE 3 g/100 mL; OCTISALATE 2 g/100 mL; AVOBENZONE 1 g/100 mL
INACTIVE INGREDIENTS: WATER; ALOE VERA LEAF; CARRAGEENAN; CHAMOMILE; SYMPHYTUM UPLANDICUM LEAF; COMFREY ROOT; TARAXACUM OFFICINALE LEAF; ECHINACEA, UNSPECIFIED; SAMBUCUS NIGRA FLOWER; AMERICAN GINSENG; MACROCYSTIS PYRIFERA; LAVANDULA ANGUSTIFOLIA FLOWERING TOP; CYMBOPOGON SCHOENANTHUS TOP; ALTHAEA OFFICINALIS ROOT; ACHILLEA MILLEFOLIUM FLOWER; GREEN TEA LEAF; PHENETHYL BENZOATE; STEARIC ACID; GLYCERYL STEARATE SE; CETYL DIMETHICONE 150; GLYCERIN; SODIUM HYDROXIDE; CETOSTEARYL ALCOHOL; POLYSORBATE 60; TRICONTANYL POVIDONE; HIGH DENSITY POLYETHYLENE; CARBOMER COPOLYMER TYPE B (ALLYL PENTAERYTHRITOL CROSSLINKED); CETYL ALCOHOL; METHYLPARABEN; DIAZOLIDINYL UREA; PROPYLPARABEN; CAPRYLYL GLYCOL

Land Shark SPF 15 Lotion

Drug Facts

Active Ingredients

Octocrylene 3.0%

Octisalate 2.0%

Avobenzone 1.0%

Purpose

Sunscreen

Uses

- helps prevent sunburn
- if used as directed with other sun protection measures (see Directions), decreases the risk of skin cancer and early skin aging caused by the sun

Warnings

For external use only

Do not use on damaged or broken skin

When using this product keep out of eyes. Rinse with water to remove.

Stop use and ask a doctor if rash occurs

Keep out of reach of children. If product is swallowed, get medical help or contact a Poison Control Center right away.

Directions

- apply liberally 15 minutes before sun exposure
- reapply:
  - after 80 minutes of swimming or sweating
  - immediately after towel drying
  - at least every 2 hours
- Sun Protection Measures. Spending time in the sun increases your risk of skin cancer and early skin aging. To decrease this risk, regularly use a sunscreen with a broad spectrum SPF 15 or higher and other sun protection measures including:
  - limit time in the sun, especially from 10 a.m. - 2 p.m.
  - wear long-sleeve shirts, pants, hats and sunglasses
- children under 6 months: Ask a doctor

Inactive Ingredients

aqueous extracts of: aloe barbadensis leaf extract, algae extract (hawaiian seaplant), chamomilla recutita (matricaria) flower extract, symphytum officinale (comfrey) root & leaf extract, taraxacum officinale (dandelion) leaf extract, echinacea purpurea (coneflower) extract, sambucus nigra (elder) flower extract, panax quinquefolium (ginseng) root extract, macrocystis pyrifera (kelp) extract, lavandula angustifolia (lavender) extract, cymbopogon schoenanthus (lemon grass) extract, althea officinalis (marshmallow) root extract, achillea millefolium (yarrow flower) extract, camellia sinensis (white tea) extract, phenethyl benzoate, octyl dodecyl citrate crosspolymer, stearic acid, glyceryl stearate se, cetyl dimethicone, glycerin, sodium hydroxide, emulsifying wax, tricontanyl-pvp, polyethylene, acrylates/c10-30 alkyl acrylates cross-polymer, cetyl alcohol, methylparaben, diazolidinyl urea, propylparaben, and caprylyl glycol.

Other Information

- protect this product from excessive cold, heat, and direct sun

Questions or comments?

Call toll free 1-800-368-7327

Principal Display Panel

192 ml NDC: 52854-915-01